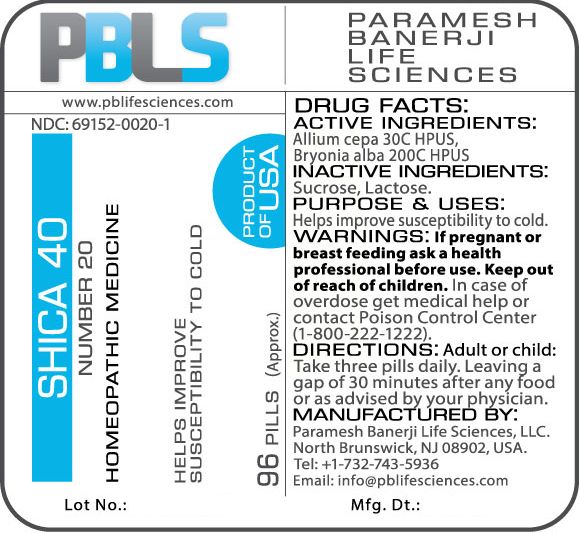 DRUG LABEL: Shica 40 Number 20
NDC: 69152-0020 | Form: PELLET
Manufacturer: Paramesh Banerji Life Sciences LLC
Category: homeopathic | Type: HUMAN OTC DRUG LABEL
Date: 20170524

ACTIVE INGREDIENTS: ONION 30 [hp_C]/1 1; BRYONIA ALBA ROOT 200 [hp_C]/1 1
INACTIVE INGREDIENTS: SUCROSE; LACTOSE

DRUG FACTS: Active Ingredients

Allium cepa 30C HPUS, Bryonia alba 200C HPUS

Inactive Ingredients

Sucrose, Lactose

Purpose

Helps improve susceptibility to cold

Uses

Helps improve susceptibility to cold

Warnings

If pregnant or breast feeding ask a health professional before use.

Keep out of reach of children. In case of overdose, get medical help or contact a Poison Control Center (1-800-222-1222) right away.

Direction

Adult or child: Take three pills daily. Leaving a gap of 30 minutes after any food or as advised by your physician.

Manufactured by

Paramesh Banerji Life Sciences, LLC.

North Brunswick, NJ 08902, USA.

Tel: +1-732-743-5936

Email: info@pblifesciences.com

Principal Display Panel

NDC: 69152-0020-1

Shica 40

Number 20

Homeopathic Medicine

Helps improve susceptibility to cold

96 Pills (Approx.)

Product of USA